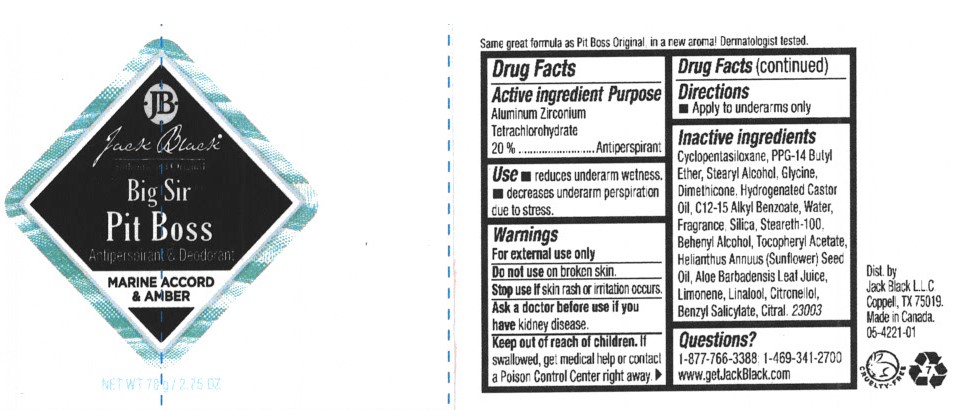 DRUG LABEL: Big Sir Pit Boss
NDC: 66738-702 | Form: STICK
Manufacturer: Jack Black L.L.C.
Category: otc | Type: HUMAN OTC DRUG LABEL
Date: 20260107

ACTIVE INGREDIENTS: ALUMINUM ZIRCONIUM TETRACHLOROHYDREX GLY 20 g/100 g
INACTIVE INGREDIENTS: STEARETH-100; DOCOSANOL; GLYCERIN; SUNFLOWER OIL; .ALPHA.-TOCOPHEROL ACETATE; ALOE VERA LEAF; CYCLOMETHICONE 5; PPG-14 BUTYL ETHER; STEARYL ALCOHOL; ALKYL (C12-15) BENZOATE; DIMETHICONE; HYDROGENATED CASTOR OIL; SILICON DIOXIDE

Jack Black Big Sir Pit Boss Antiperspirant & Deodorant

Active Ingredient

Aluminum Zirconium Tretrachlorohydex Gly 20% Anhydrous

Purpose

Antiperspirant

Uses

Reduces underarm wetness. Decreases underarm perspiration due to stress.

Warnings

For external use only. Ask a doctor before use if you have kidney disease.

Do not use on broken skin.

Stop use if skin rash or irritation occurs.

Ask a doctor before use if you hvae kidney disease.

Keep out of the reach of children.

If swallowed, get medical help or contact a Poison Control Center right away.

DOSAGE AND ADMINISTRATION

Apply to underarms only.

INACTIVE INGREDIENT

Other Ingredients:Cyclopentasiloxane, PPG-14 Butyl Ether, Stearyl Alcohol, Glycine, Dimethicone, Hydrogenated Castor Oil, C12-15 Alkyl Benzoate, Water, Fragrance, Silica, Steareth-100, Behenyl Alcohol, Tocopheryl Acetate, Helianthus Annuus (Sunflower) Seed Oil, Aloe Barbadensis Leaf Juice, Limonene, Linalool, Citronellol, Benzyl Salicylate, Citral. 23003

QUESTIONS

Questions? 1-877-766-3388; 1-469-341-2700; www.getJackBlack.com